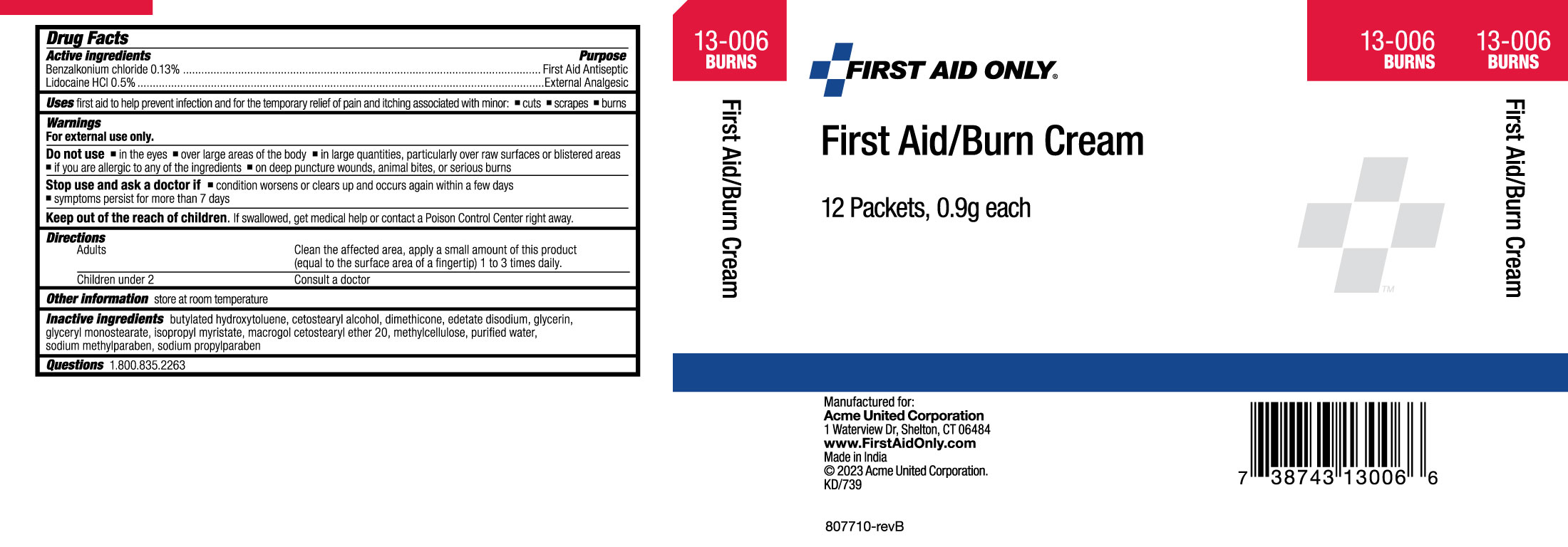 DRUG LABEL: First Aid Only First Aid/Burn
NDC: 0924-5730 | Form: CREAM
Manufacturer: Acme United Corporation
Category: otc | Type: HUMAN OTC DRUG LABEL
Date: 20231009

ACTIVE INGREDIENTS: LIDOCAINE HYDROCHLORIDE 5 mg/1 g; BENZALKONIUM CHLORIDE 1.3 mg/1 g
INACTIVE INGREDIENTS: BUTYLATED HYDROXYTOLUENE; CETOSTEARYL ALCOHOL; DIMETHICONE; GLYCERIN; GLYCERYL MONOSTEARATE; ISOPROPYL MYRISTATE; WATER; EDETATE SODIUM; METHYLPARABEN SODIUM; PROPYLPARABEN SODIUM

First Aid Only First Aid/Burn Cream

Active Ingredients

Benzalkonium chloride 0.13%

Lidocaine HCL 0.5%

Purpose

First Aid Antiseptic

External Analgesic

Uses

First aid to help prevent infection and for the temporary relief of pain and itching associated with minor: •cuts, •scrapes, •burns.

Warnings

For external use only.

Do not use

▪in the eyes ▪over large areas of the body ▪in large quantities, particularly over raw surfaces or blistered areas ▪if you are allergic to any of the ingredients ▪on deep puncture wounds, animal bites, or serious burns

Stop use and ask a doctor if

▪condition worsens or clears up and occurs again within a few days ▪symptoms persist for more than 7 days

Keep out of reach of children.

If swallowed, get medical help or contact a Poison Control Center right away.

Directions

Adults - Clean the affected area, apply a small amount of product (equal to the surface area of a fingertip) 1 to 3 times daily.

Children under 2- Consult a doctor

Other Information

Store at room temperature

Inactive Ingredients

butylated hydroxytoluene, cetostearyl alcohol, dimethicone, edetate sodium, glycerin, glyceryl monostearate, isopropyl myristate, macrogol cetostearyl ether 20, methylcellulose, purified water, sodium methylparaben, sodium propylparaben

Questions

1.800.835.2263

Carton Label